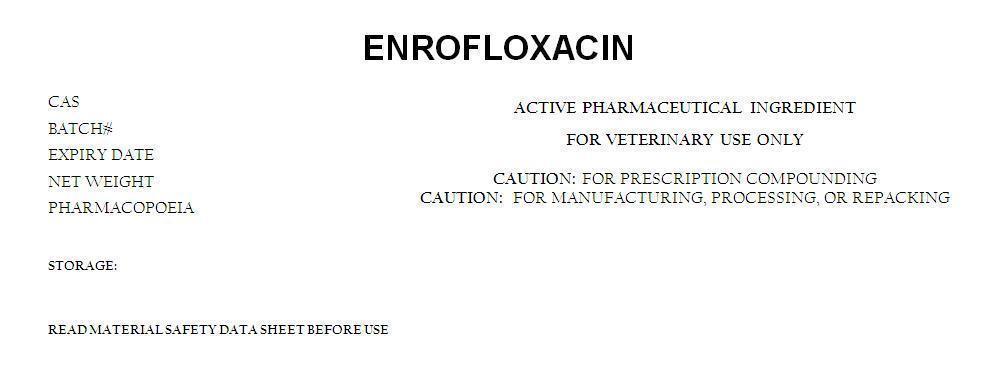 DRUG LABEL: ENROFLOXACIN
NDC: 62448-931 | Form: POWDER
Manufacturer: BOSTON SYNTHETICS LIMITED
Category: other | Type: BULK INGREDIENT
Date: 20141124

ACTIVE INGREDIENTS: ENROFLOXACIN 1 g/1 g

ENROFLOXACIN